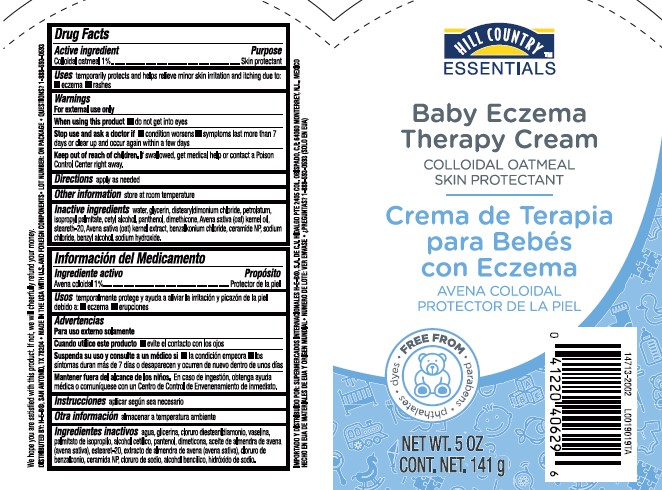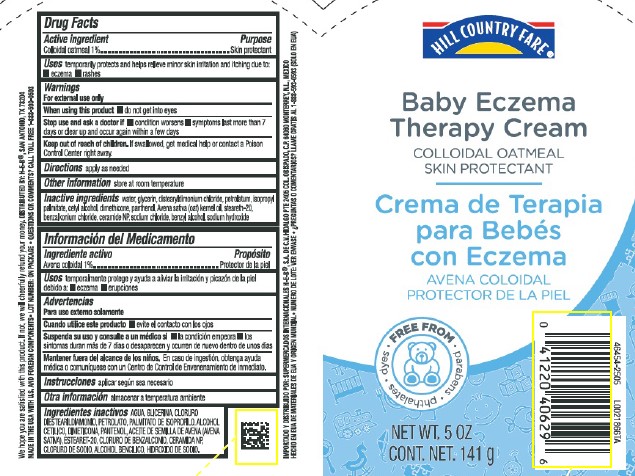 DRUG LABEL: Colloidal oatmeal
NDC: 37808-128 | Form: CREAM
Manufacturer: H E B
Category: otc | Type: HUMAN OTC DRUG LABEL
Date: 20260224

ACTIVE INGREDIENTS: OATMEAL 10 mg/1 g
INACTIVE INGREDIENTS: WATER; GLYCERIN; DISTEARYLDIMONIUM CHLORIDE; PETROLATUM; ISOPROPYL PALMITATE; CETYL ALCOHOL; DIMETHICONE, UNSPECIFIED; PANTHENOL; OAT KERNEL OIL; STEARETH-20; BENZALKONIUM CHLORIDE; CERAMIDE NP; SODIUM CHLORIDE; BENZYL ALCOHOL; SODIUM HYDROXIDE

HEB Hill Country_HCF 601.001/601AC
Baby Eczema Therapy Cream

Active ingredient

Colloidal oatmeal 1%

Purpose

Skin protectant

Uses

temporarily protects and helps relieve minor skin irritation and itching due to:

- eczema
- rashes

Warnings

For external use only

When using this product

- do not get into eyes

Stop use and ask a doctor if

- condition worsens
- symptoms last more than 7 days or clear up and occur again within a few days

Keep out of reach of children.

If swallowed, get medical help or contact a Poison Control Center right away.

Directions

apply as needed

Other information

store at room temperature

Inactive ingredients

water, glycerin, distearyldimonium chloride, petrolatum, isopropyl palmitate, cetyl alcohol, dimethicone, panthenol, Avena sativa (oat) kernel oil, steareth-20, benzalkonium chloride, ceramide NP, sodium chloride, benzyl alcohol, sodium hydroxide

adverse reactions

We hope you are satisfied with this product. If not, we will cheerfully refund your money.

DISTRIBUTED BY: H-E-B®, SAN ANTONIO, TX 78204

MADE IN THE USA WTH U.S. AND FOREIGN COMPONENTS

LOT NUMBER: ON PACKAGE

QUESTIONS OR COMMENTS? CALL TOLL FREE 1-888-593-0593

principal display panel

HILL COUNTRY™

ESSENTIALS

Baby Eczema

Therapy Cream

COLLOIDAL OATMEAL

SKIN PROTECTANT

FREE FROM

- parabens
- phthalates
- dyes

NET WT. 5 OZ CONT. NET. 141 g

PRINCIPAL DISPLAY PANEL

HILL COUNTRY FARE®

Baby Eczema

Therapy Cream

COLLOIDAL OATMEAL

SKIN PROTECTANT

FREE FROM

- parabens
- phthalates
- dyes

NET WT. 5 OZ CONT. NET. 141 g